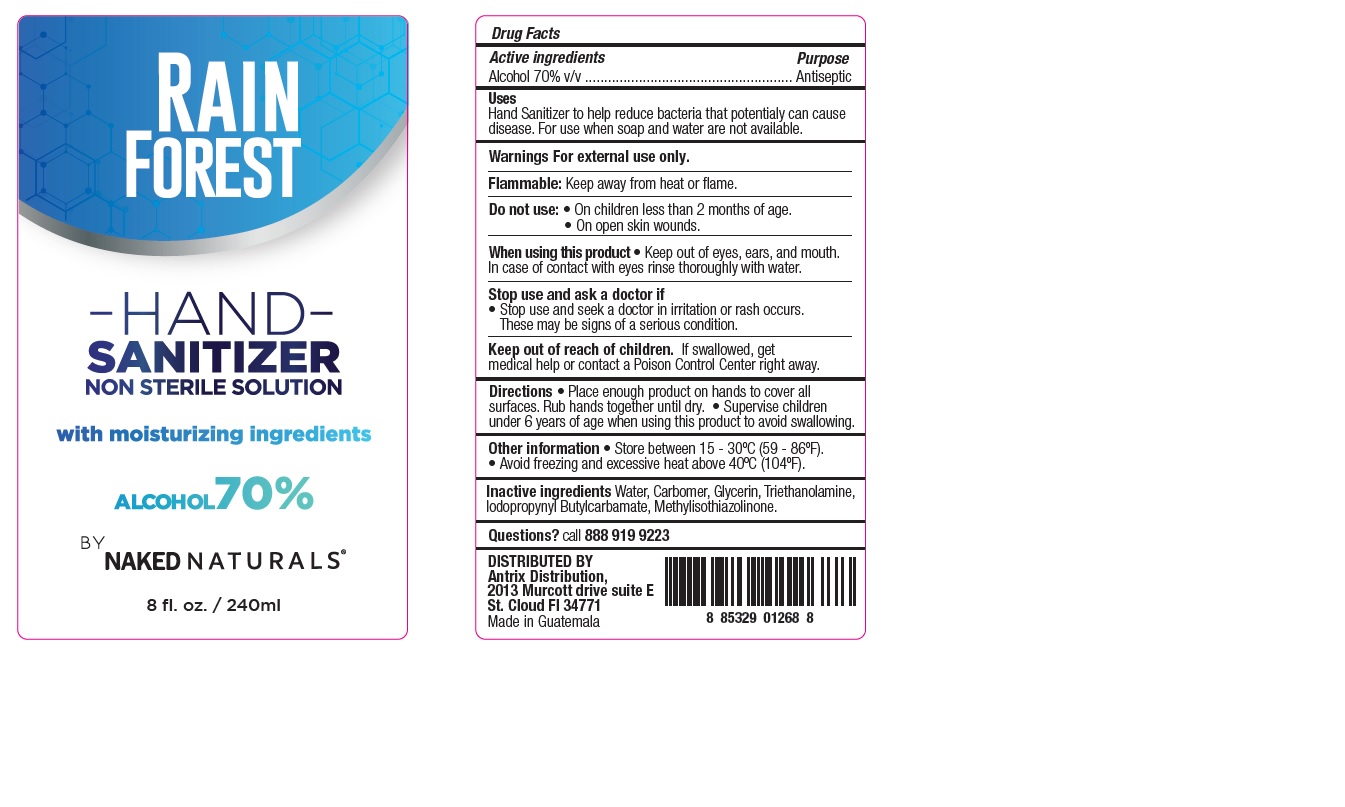 DRUG LABEL: RAIN FOREST HAND SANITIZER
NDC: 77646-001 | Form: GEL
Manufacturer: Antrix Distribution LLC
Category: otc | Type: HUMAN OTC DRUG LABEL
Date: 20200512

ACTIVE INGREDIENTS: ALCOHOL 70 mL/100 mL
INACTIVE INGREDIENTS: GLYCERIN; CARBOMER HOMOPOLYMER, UNSPECIFIED TYPE; METHYLISOTHIAZOLINONE; IODOPROPYNYL BUTYLCARBAMATE; TROLAMINE; WATER

Rain Forest Hand Sanitizer - Antrix

Active ingredients

Alcohol 70% v/v

Purpose

Antiseptic

Uses

Hand Sanitizer to help reduce bacteria that potentially can cause disease. For use when soap and water are not available.

Warnings

For external use only.

Flammable. Keep away from heat or flame.

Do not use

- On children less than 2 months of age.
- On open skin wounds.

When using this product

- Keep out of eyes, ears and mouth. In case of contact with eyes rinse thoroughly with water.

Stop use and ask a doctor if

- Stop use and seek a doctor if irritation or rash occurs. These may be signs of a serious condition.

Keep out of reach of children.

If swallowed, get medical help or contact a Poison Control Center right away.

Directions

- Place enough product on hands to cover all surfaces. Rub hands together until dry.
- Supervise children under 6 years of age when using this product to avoid swallowing.

Other information

- Store between 15-30C (59-86F).
- Avoid freezing and excessive heat above 40C (104F)

Inactive ingredients

Water, Carbomer, Glycerin, Triethanolamine, Iodopropynyl Butylcarbamate, Methylisothiazolinone.

Questions?

call 888 919 9223

Company Information

DISTRIBUTED BY

Antrix Distribution,

2013 Murcott drive suite E

St. Cloud Fl 34771

Made in Guatemala

Product Packaging - 240 ml

RAIN

FOREST

HAND

SANITIZER

NON STERILE SOLUTION

with moisturizing ingredients

ALCOHOL 70%

BY

NAKED NATURALS

8 fl. oz. / 240ml